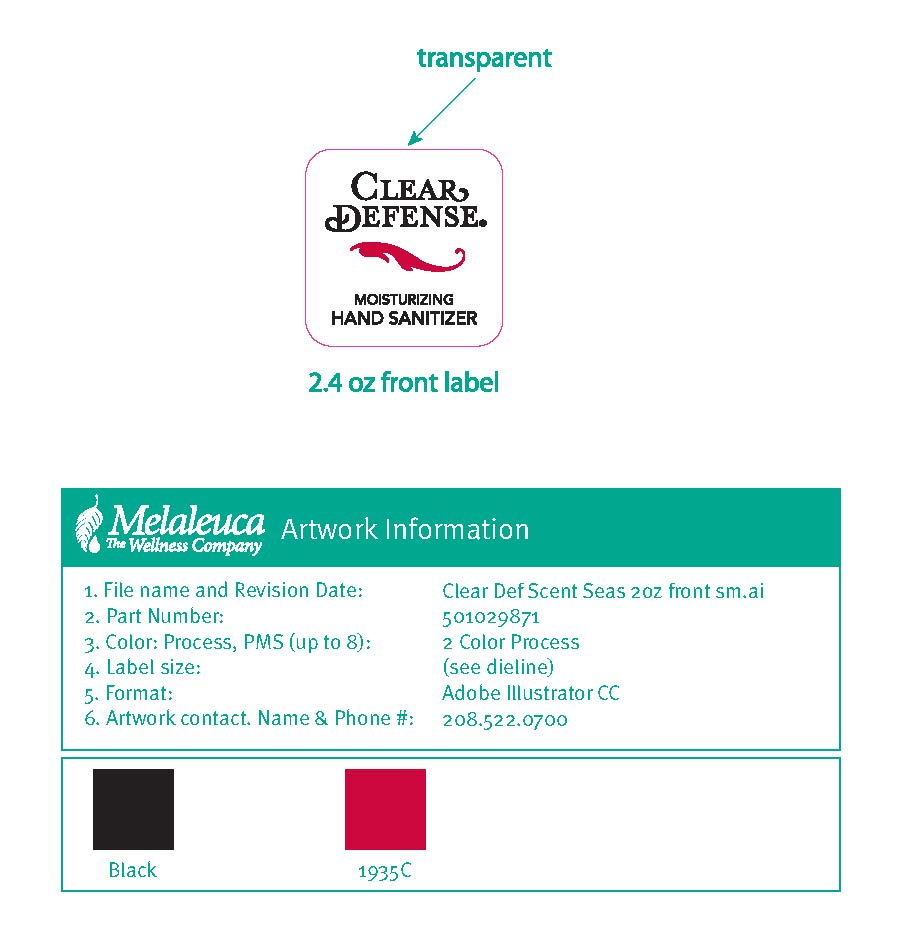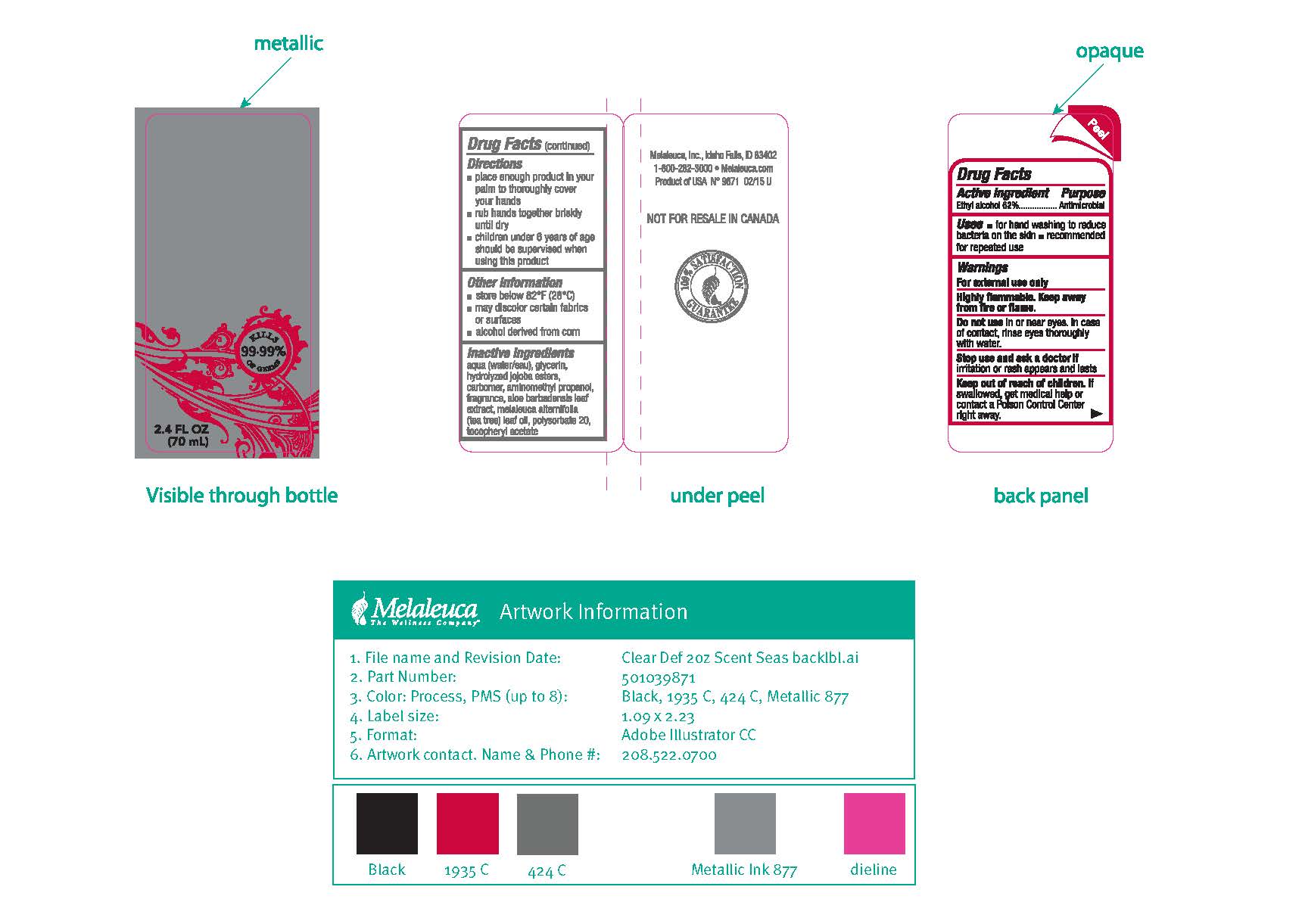 DRUG LABEL: Clear Defense
NDC: 54473-271 | Form: GEL
Manufacturer: Melaleuca Inc
Category: otc | Type: HUMAN OTC DRUG LABEL
Date: 20180329

ACTIVE INGREDIENTS: ALCOHOL 36.58 g/59 mL
INACTIVE INGREDIENTS: .ALPHA.-TOCOPHEROL ACETATE; ALOE VERA LEAF; AMINOMETHYLPROPANOL; ANHYDROXYLITOL; CARBOMER HOMOPOLYMER TYPE C (ALLYL PENTAERYTHRITOL CROSSLINKED); COCOA BUTTER; FD&C BLUE NO. 1; GLYCERIN; MANGIFERA INDICA SEED BUTTER; POLYSORBATE 20; FD&C YELLOW NO. 5; SHEA BUTTER; TITANIUM DIOXIDE; TEA TREE OIL; WATER; XYLITOL; XYLITYLGLUCOSIDE

Clear Defense Maui Melon

Active ingredient

Ethyl alcohol 62%

Purpose

Antimicrobial

Uses

■ for handwashing to reduce bacteria on the skin

■ recommended for repeated use

Warnings: For external use only

Do not use in or near eyes. In case of contact, rinse eyes thoroughly with water.

Stop use and ask a doctor if irritation or rash appears and lasts

Keep out of reach of children. If swallowed, get medical help or contact a Poison Control Center right away.

DOSAGE AND ADMINISTRATION

Directions ■ place enough product in your palm to thoroughly cover your hands ■ rub hands together briskly until dry ■ children under 6 years of age should be supervised when using this product

Other information ■ store below 82°F (28°C) ■ may discolor certain fabrics or surfaces ■ alcohol derived from corn

INACTIVE INGREDIENT

Inactive ingredients water, gylcerin, xylitol, anhydroxylitol, xylitylglucoside, carbomer, aminomethyl propanol, fragrance, aloe barbadensis leaf extract, melaleuca alternifolia leaf oil, polysorbate 20, tocopheryl acetate, jojoba esters, butyrospermum parkii, theobroma cacao seed butter, mangifera indica seed butter, blue 1 lake, titanium dioxide, yellow 5 lake